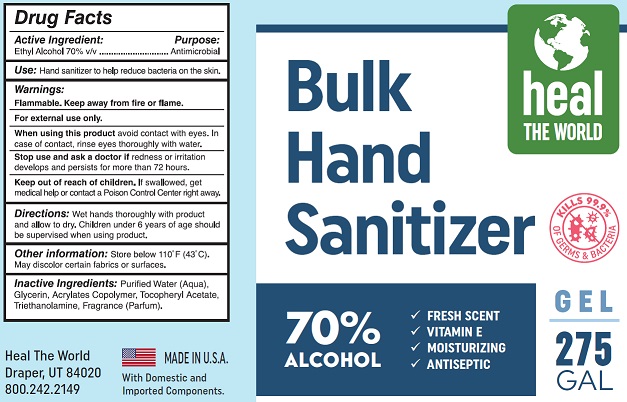 DRUG LABEL: Bulk Hand Sanitizer
NDC: 73973-001 | Form: GEL
Manufacturer: HEAL THE WORLD, LLC
Category: otc | Type: HUMAN OTC DRUG LABEL
Date: 20200603

ACTIVE INGREDIENTS: ALCOHOL 70 mL/100 mL
INACTIVE INGREDIENTS: WATER; GLYCERIN; ACRYLATE/ISOBUTYL METHACRYLATE/N-TERT-OCTYLACRYLAMIDE COPOLYMER (75000 MW); .ALPHA.-TOCOPHEROL ACETATE; TROLAMINE

Active Ingredient

Ethyl Alcohol 70% v/v.

Purpose

Antimicrobial

Use

Hand sanitizer to help reduce bacteria on the skin.

Warnings

Flammable. Keep away from fire or flame.
For external use only.
When using this product avoid contact with eyes. In case of contact, rinse eyes thoroughly with water.
Stop use and ask a doctor if redness or irritation develops and persists for more than 72 hours.

Keep out of reach of children. If swallowed, get medical help or contact a Poison Control Center right away.

Directions

Wet hands thoroughly with product and allow to dry.

Children under 6 years of age should be supervised when using product.

Other information

Store below 110° F (43° C). May discolor certain fabrics or surfaces.

Inactive ingredients

Purified Water (Aqua), Glycerin, Acrylates Copolymer, Tocopherol Acetate, Triethanolamine, Fragrance (Parfum)